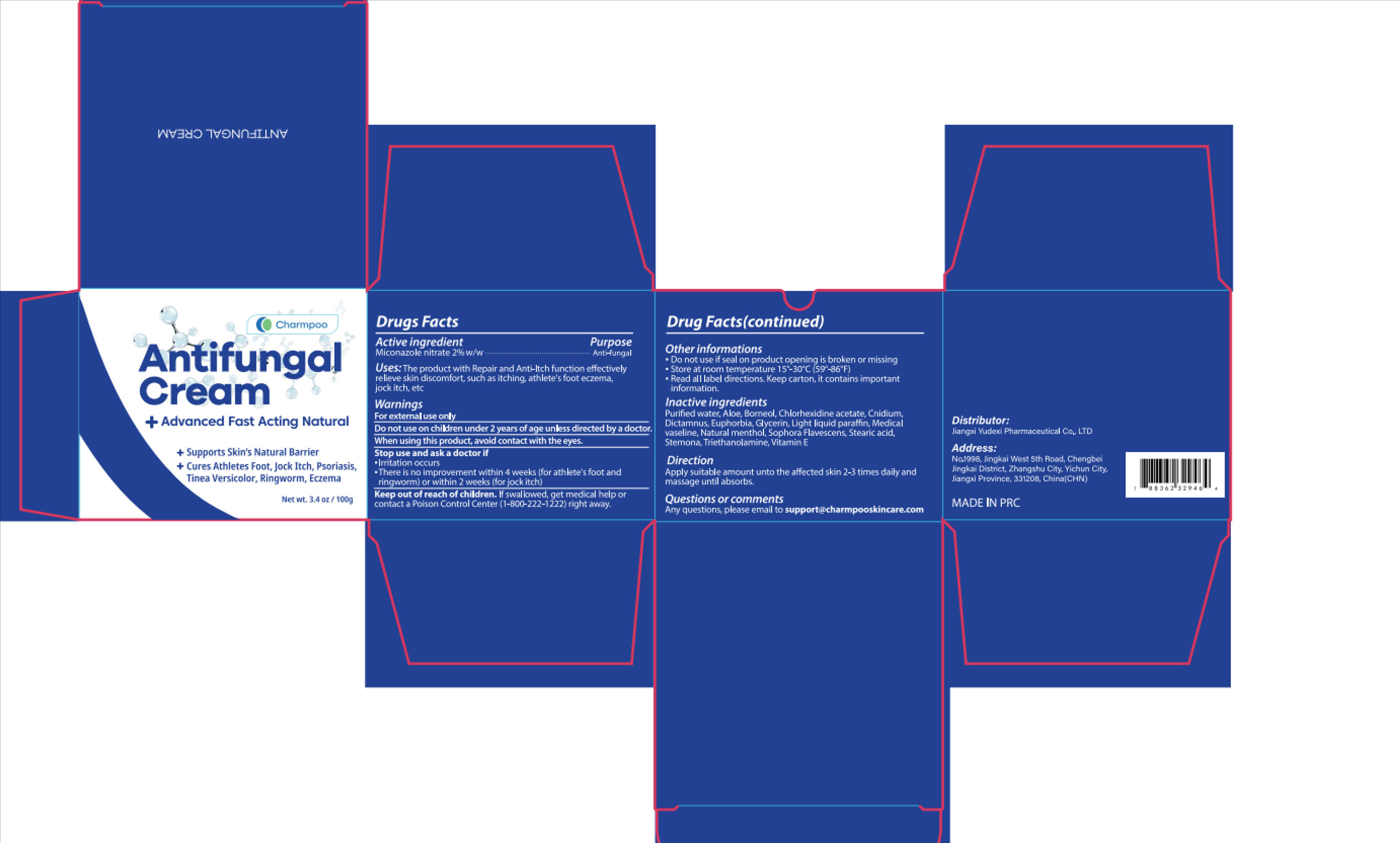 DRUG LABEL: Charmpoo Antifungal Cream
NDC: 85248-142 | Form: CREAM
Manufacturer: Jiangxi Yudexi Pharmaceutical Co., LTD
Category: otc | Type: HUMAN OTC DRUG LABEL
Date: 20260214

ACTIVE INGREDIENTS: MICONAZOLE NITRATE 2 g/100 g
INACTIVE INGREDIENTS: WATER; MENTHOL; SOPHORA FLAVESCENS ROOT; .ALPHA.-TOCOPHEROL; LIGHT MINERAL OIL; ALOE; BORNEOL; CHLORHEXIDINE ACETATE; GLYCERIN; VASICINONE; STEMONA JAPONICA ROOT; TRIETHANOLAMINE; DICTAMNUS DASYCARPUS ROOT; CNIDIUM MONNIERI FRUIT; EUPHORBIA NERIIFOLIA LEAF; STEARIC ACID

85248-142

Active Ingredient

miconazole nitrate 2% w/w

Purpose

Anti-fungal

Use

The product with Repair and Anti-ltch function effectively relieve skin discomfort, such as itching, athlete's foot eczema, jock itch, etc

Warnings

For external use only

Do not use

children under 2 years of age unless directed by a doctor.

When Using

avoid contact with the eyes.

Stop Use

·Irritation occurs ·There is no improvement within 4 weeks (for athlete's foot and fingworm) or within 2 weeks (for jock itch)

Ask Doctor

·Irritation occurs ·There is no improvement within 4 weeks (for athlete's foot and fingworm) or within 2 weeks (for jock itch)

Keep Oot Of Reach Of Children

lf swallowed, get medical help or contact a Poison controlcenter(1-800-222-1222)right away.

Directions

Apply suitable amount unto the affected skin 2-3 times daily and massage until absorbs.

Other information

·Do not use if seal on product opening is broken or missing ·Store at room temperature 15°-30°C(59°-86°F) ·Read all label directions. Keep carton, it contains important information.

Inactive ingredients

Purifed water, Aloe, Borneol, Chlorhexidine acetate, Cnidium, Dictamnus,Euphorbia, Glycerin, Lightliquid paraffn, Medical vaseline, Natural menthol Sophora Flavescens, Stearic acid, Stemona,Triethanolamine, Vitamin E